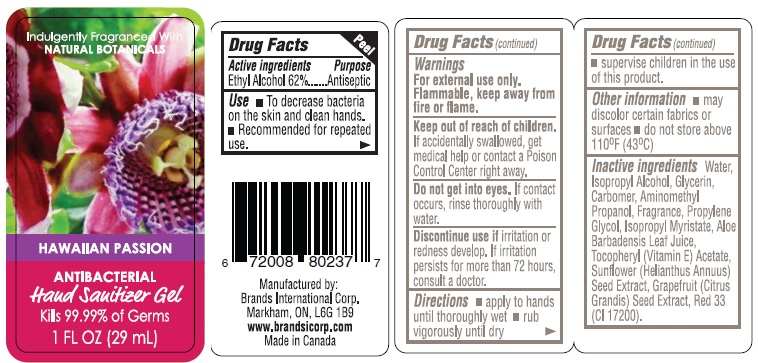 DRUG LABEL: Hawaiian Passion Hand Sanitizer

NDC: 50157-106 | Form: SOLUTION
Manufacturer: Brands International
Category: otc | Type: HUMAN OTC DRUG LABEL
Date: 20150421

ACTIVE INGREDIENTS: ALCOHOL 62 mL/100 mL
INACTIVE INGREDIENTS: WATER; ISOPROPYL ALCOHOL; GLYCERIN; CARBOMER HOMOPOLYMER TYPE C (ALLYL PENTAERYTHRITOL CROSSLINKED); AMINOMETHYLPROPANOL; PROPYLENE GLYCOL; ISOPROPYL MYRISTATE; ALOE VERA LEAF; .ALPHA.-TOCOPHEROL ACETATE; SUNFLOWER SEED; CITRUS PARADISI SEED; D&C RED NO. 33

Hawaiian Passion Hand Sanitizer

Drug Facts

Active Ingredients

Ethyl Alcohol 62%

Purpose

Antiseptic

Uses

- To decrease bacteria on the skin and clean hands.
- Recommended for repeated use.

Warnings

For external use only.

Flammable. Keep away from fire or flame.

Keep out of reach of children. If accidentally swallowed, get medical help or contact a Poison Control Center right away.

WHEN USING

Do not get into eyes. If contact occurs, rinse thoroughly with water.

STOP USE

Discontinue use if irritation or redness develop. If irritation persists for more than 72 hours, consult a doctor.

Directions

- apply to hands until thoroughly wet
- rub vigorously until dry
- supervise children in the use of this product.

Other information

- may discolor certain fabrics or surfaces.
- do not store above 110°F (43°C)

Inactive ingredients

Water, Isopropyl Alcohol, Glycerin, Carbomer, Aminomethyl Propanol, Fragrance, Propylene Glycol, Isopropyl Myristate, Aloe Barbadensis Leaf Juice, Tocopheryl (Vitamin E) Acetate, Sunflower (Helianthus Annus) Seed Extract, Grapefruit (Citrus Grandis) Seed Extract, Red 33 (CI 17200).

Manufactured by:

Brands International Corp.
Markham, ON, L6G 1B9 Canada
www.brandsicorp.com

Package Label

HAWAIIAN PASSION

ANTIBACTERIAL

Hand Sanitizer Gel

Kills 99.99% of Germs
1 FL OZ (29 ml)